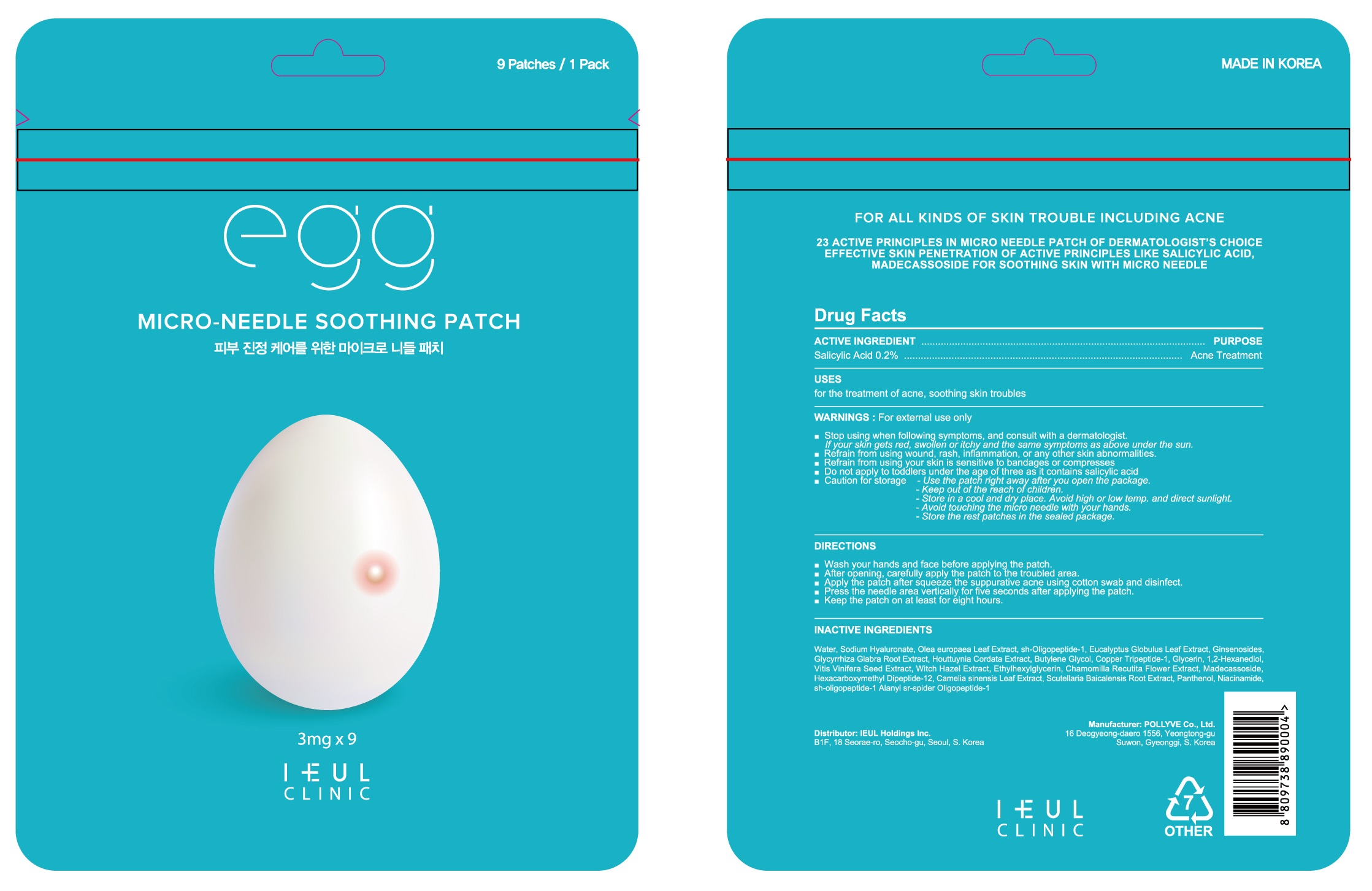 DRUG LABEL: Egg micro needle soothing
NDC: 80559-010 | Form: PATCH
Manufacturer: IEUL Holdings Inc.
Category: otc | Type: HUMAN OTC DRUG LABEL
Date: 20210105

ACTIVE INGREDIENTS: Salicylic Acid 0.002 1/1 1
INACTIVE INGREDIENTS: Water; Butylene Glycol; Glycerin

ACTIVE INGREDIENT

Salicylic Acid 0.2%

INACTIVE INGREDIENTS

Water, Sodium Hyaluronate, Olea europaea Leaf Extract, sh-Oligopeptide-1, Eucalyptus Globulus Leaf Extract, Houttuynia Cordata Extract, Butylene Glycol, Glycyrrhiza Glabra Root Extract, Panthenol, Glycerin, Madecassoside, Niacinamide, Vitis Vinifera Seed Extract, Witch Hazel Extract, Camelia sinensis Leaf Extract, 1,2-Hexanediol, Ginsenosides, Ethylhexylglycerin, Scutellaria Baicalensis Root Extract, Chamomilla Recutita Flower Extract, Hexacarboxymethyl Dipeptide-12, Pentasodium Tetracarboxymethyl heptadecanoyl dipeptide-12, Copper Tripeptide-1, sh-oligopeptide-1 Alanyl sr-spider

PURPOSE

Acne Treatment

WARNINGS

For external use only

■ Stop using when following symptoms, and consult with a dermatologist.
● If your skin gets red, swollen or itchy and the same symptoms as above under the sun.
■ Refrain from using wound, rash, inflammation, or any other skin abnormalities.
■ Refrain from using your skin is sensitive to bandages or compresses
■ Do not apply to toddlers under the age of three as it contains salicylic acid
■ Caution for storage
● Use the patch right away after you open the package
● Keep out of the reach of children
● Store in a cool and dry place. Avoid high or low temp. and direct sunlight
● Avoid touching the micro needle with your hands
● Store the rest patches in the sealed package

KEEP OUT OF REACH OF CHILDREN

Uses

for the treatment of acne, soothing skin troubles

Directions

■ Wash your hands and face before applying the patch
■ After opening, carefully apply the patch to the troubled area
■ Apply the patch after squeeze the suppurative acne using cotton swab and disinfect
■ Press the needle area vertically for five seconds after applying the patch
■ Keep the patch on at least for eight hours.